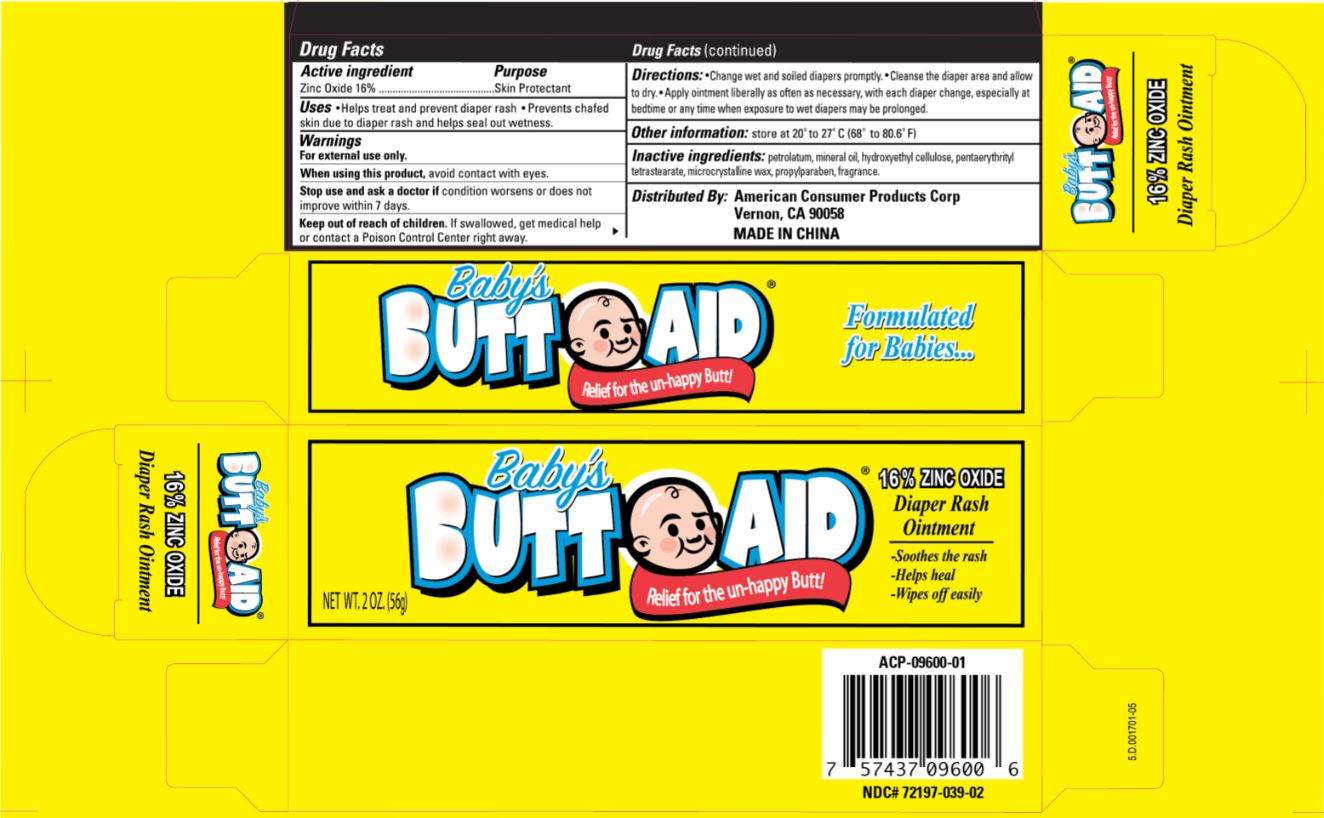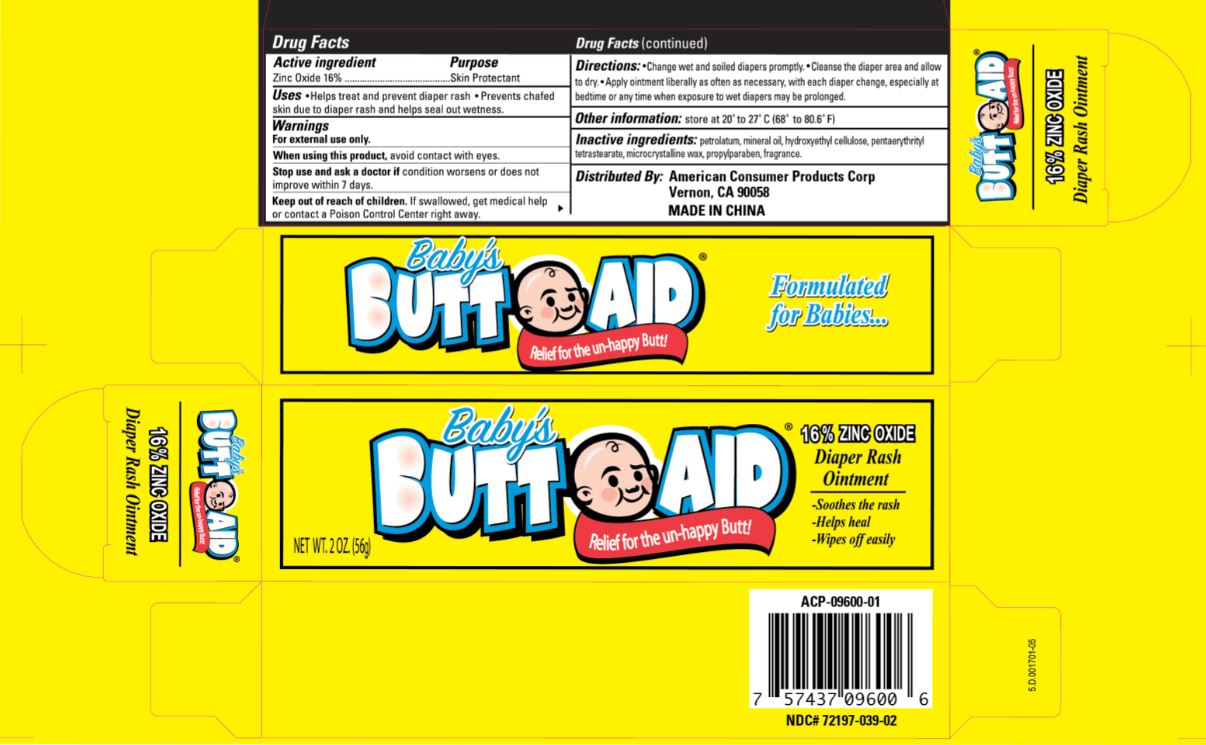 DRUG LABEL: Babys Butt Aid
NDC: 72197-039 | Form: OINTMENT
Manufacturer: American Consumer Products Corp
Category: otc | Type: HUMAN OTC DRUG LABEL
Date: 20210310

ACTIVE INGREDIENTS: ZINC OXIDE 16 g/100 g
INACTIVE INGREDIENTS: PENTAERYTHRITYL TETRASTEARATE; MINERAL OIL; MICROCRYSTALLINE WAX; PETROLATUM; HYDROXYETHYL CELLULOSE, UNSPECIFIED; PROPYLPARABEN

Babys Butt Aid

Active Ingredient

Zinc Oxide 16%

Purpose

Skin Protectant

Uses

Uses • Helps treat and prevent diaper rash • Prevents chafed skin due to diaper rash and helps seal out wetness.

Warnings

For external use only.

When using this product, avoid contact with eyes.

Stop use and ask a doctor if condition worsens or does not improve within 7 days.

Keep out of reach of children. If swallowed, get medical help or contact a Poison Control Center right away.

Directions

Directions: • Change wet and soiled diapers promptly. • Cleanse the diaper area and allow to dry. • Apply ointment liberally as often as necessary, with each diaper change, especially at bedtime or any time when exposure to wet diapers may be prolonged.

Other information

Other information: store at 20° to 27°C (68° to 80.6°F)

Inactive ingredients

Inactive ingredients: petrolatum, mineral oil, hydroxyethyl cellulose, pentaerythrityl tetrastearate, microcrystalline wax, propylparaben, fragrance.

Distributed By:

Distributed By: American Consumer Products Corp

Vernon, CA 90058

MADE IN CHINA